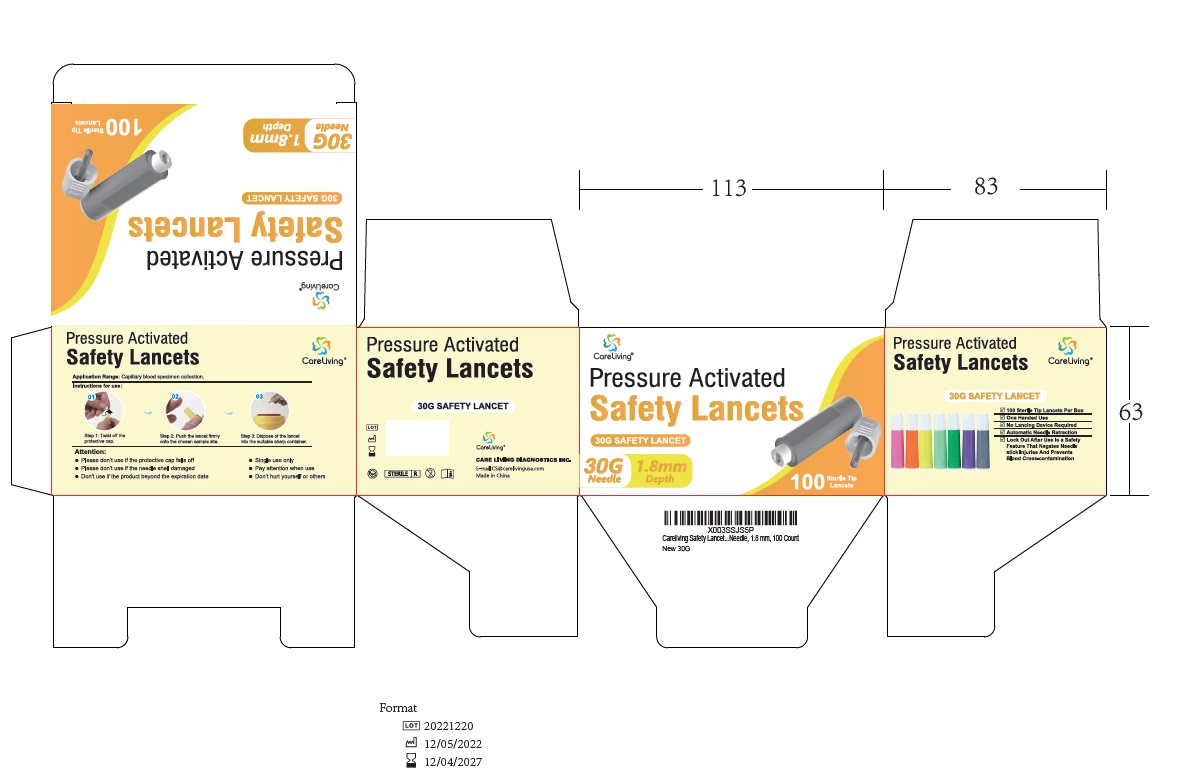 DRUG LABEL: Pressure Activated Safety Lancet
NDC: 83568-001
Manufacturer: CARE LIVING DIAGNOSTICS INC.
Category: other | Type: MEDICAL DEVICE
Date: 20230907

Pressure Activated Safety Lancet 30G

Name

Pressure Activated Lancet